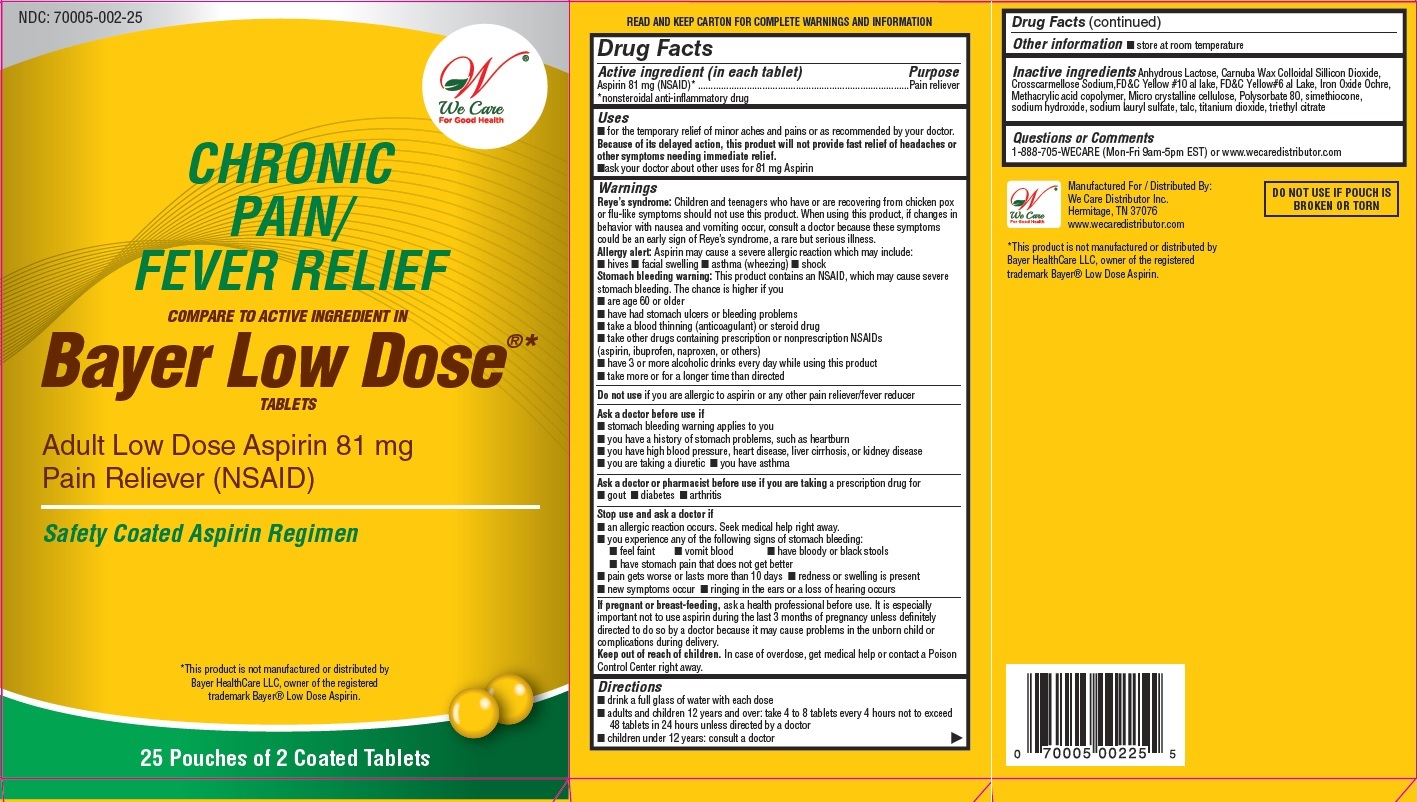 DRUG LABEL: Chronic Pain/Fever Relief
NDC: 70005-002 | Form: TABLET
Manufacturer: We Care Distributor Inc.
Category: otc | Type: HUMAN OTC DRUG LABEL
Date: 20160301

ACTIVE INGREDIENTS: Aspirin 81 mg/1 1
INACTIVE INGREDIENTS: CARNAUBA WAX; ANHYDROUS LACTOSE; CROSCARMELLOSE SODIUM; D&C YELLOW NO. 10; FD&C YELLOW NO. 6; BROWN IRON OXIDE; METHACRYLIC ACID; CELLULOSE, MICROCRYSTALLINE; POLYSORBATE 80; DIMETHICONE; SODIUM HYDROXIDE; SODIUM LAURYL SULFATE; TITANIUM DIOXIDE; TALC; TRIETHYL CITRATE

Chronic Pain/Fever Relief - Aspirin Delayed Release Tablets, 81 mg

Drug Facts

ACTIVE INGREDIENT

Active Ingredient (in each tablet) | Purpose
Aspirin 81 mg (NSAID*) | Pain reliever
*nonsteroidal anti-inflammatory drug

Uses

- for the temporary relief of minor aches and pains or as recommended by your doctor. Because of its delayed action, this product will not provide fast relief of headaches or other symptoms needing immediate relief.
- ask your doctor about other uses for 81 mg Aspirin

Warnings

Reye's syndrome

Children and teenagers who have or are recovering from chicken pox or flu-like symptoms should not use this product. When using this product, if changes in behavior with nausea and vomiting occur, consult a doctor because these symptoms could be an early sign of Reye's syndrome, a rare but serious illness.

Allergy alert

Aspirin may cause a severe allergic reaction which may include:

- hives
- facial swelling
- asthma (wheezing)
- shock

Stomach bleeding warning

This product contains an NSAID, which may cause severe stomach bleeding. The chance is higher if you

- are age 60 or older
- have had stomach ulcers or bleeding problems
- take a blood thinning (anticoagulant) or steroid drug
- take other drugs containing prescription or nonprescription NSAIDs (aspirin, ibuprofen, naproxen, or others)
- have 3 or more alcoholic drinks every day while using this product
- take more or for a longer time than directed

Do not use

- if you are allergic to aspirin or any other pain reliever/fever reducer

Ask a doctor before use if

- stomach bleeding warning applies to you
- you have a history of stomach problems, such as heartburn
- you have high blood pressure, heart disease, liver cirrhosis, or kidney disease
- you are taking a diuretic
- you have asthma

Ask a doctor or pharmacist before use if you are taking

- a prescription drug for diabetes, gout, or arthritis

Stop use and ask a doctor if

- an allergic reaction occurs. Seek medical help right away.
- you experience any of the following signs of stomach bleeding:
-
  - feel faint
  - vomit blood
  - have bloody or black stools
  - have stomach pain that does not get better
  - pain gets worse or lasts for more than 10 days
  - redness or swelling is present
  - any new symptoms occur
  - ringing in the ears or loss of hearing occurs

PREGNANCY OR BREAST FEEDING

If pregnant or breast-feeding, ask a health professional before use. It is especially important not to use aspirin during the last 3 months of pregnancy unless definitely directed to do so by a doctor because it may cause problems in the unborn child or complications during delivery.

Keep out of reach of children.

In case of overdose, get medical help or contact a Poison Control Center (1-800-222-1222) right away. Quick medical attention is critical for adults as well as for children even if you do not notice any signs or symptoms.

Directions

- drink a full glass of water with each dose
- adults and children 12 years and over: take 4 to 8 tablets every 4 hours; not to exceed 48 tablets in 24 hours unless directed by a doctor
- children under 12 years: consult a doctor

Other information

- store at room temperature
- read all product information before using. Keep this box for important information

Inactive ingredients

Anhydrous Lactose, Carnuba Wax Colloidal Sillicon Dioxide, Crosscarmellose Sodium,FD&C Yellow #10 al lake, FD&C Yellow#6 al Lake, Iron Oxide Ochre, Methacrylic acid copolymer, Micro crystalline cellulose, Polysorbate 80, simethiocone, sodium hydroxide, sodium lauryl sulfate, talc, titanium dioxide, triethyl citrate

Questions or comments?

1-888-705-WECARE (Mon-Fri 9am-5pm EST) or www.wecaredistributor.com

PRINCIPAL DISPLAY PANEL

See New Warnings Information & Directions

Compare to the Active Ingredients in
Bayer Low Dose

Aspirin Delayed Release Tablets, 81 mg

TO OPEN
PUSH IN TAB AND PULL OUT

25 Pouches of 2 Caplets Each